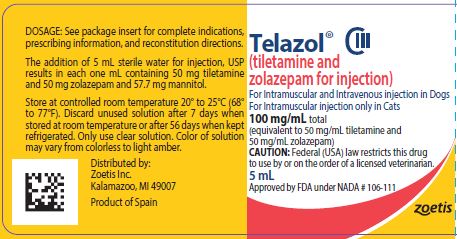 DRUG LABEL: Telazol
NDC: 54771-9050 | Form: INJECTION, POWDER, FOR SOLUTION
Manufacturer: Zoetis Inc.
Category: animal | Type: PRESCRIPTION ANIMAL DRUG LABEL
Date: 20230911
DEA Schedule: CIII

ACTIVE INGREDIENTS: TILETAMINE HYDROCHLORIDE 50 mg/1 mL; ZOLAZEPAM HYDROCHLORIDE 50 mg/1 mL
INACTIVE INGREDIENTS: MANNITOL 57.7 mg/1 mL

Telazol® CIII
(tiletamine and zolazepam for injection)

100 mg/mL total
(equivalent to 50 mg/mL tiletamine and 50 mg/mL zolazepam)
For Intramuscular and Intravenous injection in Dogs
For Intramuscular injection only in Cats

CAUTION

Federal (USA) law restricts this drug to use by or on the order of a licensed veterinarian.

DESCRIPTION

TELAZOL (tiletamine and zolazepam for injection) is a nonnarcotic, nonbarbiturate, injectable anesthetic agent for dogs and cats. Chemically, TELAZOL is a combination of equal parts by weight of base of tiletamine hydrochloride (2-[ethylamino]-2-[2-thienyl]-cyclohexanone hydrochloride), an arylaminocycloalkanone dissociative anesthetic, and zolazepam hydrochloride (4-[o-fluorophenyl]-6, 8-dihydro-1,3,8- trimethylpyrazolo [3, 4-e][1,4] diazepin-7 [1H]-1- hydrochloride), a nonphenothiazine diazepinone having minor tranquilizing properties. The product is supplied sterile in vials. The addition of 5 mL diluent produces a solution containing the equivalent of 50 mg tiletamine base, 50 mg zolazepam base and 57.7 mg mannitol per milliliter. This solution has a pH of 2 to 3.5 and is recommended for deep intramuscular injection.

INDICATIONS

Dogs
TELAZOL is indicated in dogs for restraint and minor procedures of short duration (30 min. avg.) requiring mild to moderate analgesia. Minor surgery is considered to be laceration repair, draining of abscesses, castrations and other procedures requiring mild to moderate analgesia. (See Dogs under Dosage and Administration.) TELAZOL administered intravenously is indicated in dogs for induction of anesthesia followed by maintenance with an inhalant anesthetic.
Cats
TELAZOL is indicated in cats for restraint or for anesthesia combined with muscle relaxation.

DOSAGE AND ADMINISTRATION

The dose is determined by the total combined concentration of 100 mg/mL (see HOW SUPPLIED)

Dogs

Intramuscular (IM) For Restraint and Minor
Procedures of Short Duration Requiring Mild to
Moderate Analgesia:
In healthy dogs, an initial intramuscular
dosage of 3 to 4.5 mg/lb (6.6 to 9.9 mg/kg)
TELAZOL is recommended for diagnostic
purposes; 4.5 to 6 mg/lb (9.9 to 13.2 mg/
kg) for minor procedures of short duration,
such as treatment of lacerations and wounds,
castrations and other procedures requiring mild
to moderate analgesia. When supplemental
doses of TELAZOL are required, such individual
supplemental doses should be less than the
initial dose, and the total dose given (initial
dose plus supplemental dose or doses)
should not exceed 12 mg/lb (26.4 mg/kg). The
maximum safe dose is 13.6 mg/lb (29.92 mg/
kg). (See Animal Safety.) Results from TELAZOL
anesthesia in dogs will be more satisfactory
if the procedures are completed within one
hour and if the procedures can be completed
following single dose administration. In order to
maintain at least a 2X margin of safety in dogs,
the use of this product is limited to procedures
that call for low doses (see Indications). Studies
show that there is variation in response to
different dosages of TELAZOL and that low
doses do not give adequate levels of anesthesia,
and in some instances do not give adequate
analgesia, for extensive procedures.

Intravenous (IV) For Induction of Anesthesia
Followed by Maintenance with an Inhalant
Anesthetic:
In dogs, for induction of anesthesia, administer
TELAZOL intravenously at 1-2 mg/lb (2.2-4.4 mg/
kg) body weight to effect. TELAZOL should be
administered slowly, over 30-45 seconds; after
approximately 30-60 seconds, the dog’s level
of consciousness, muscle relaxation, and jaw
tone should be assessed to determine the
ability to intubate. If after waiting 60 seconds
the dog’s level of anesthesia is not sufficient for
successful intubation, additional TELAZOL may be
administered; the total dose should not exceed
2 mg/lb (4.4 mg/kg) body weight.

Cats

In healthy cats, an initial TELAZOL dosage of 4.4 to
5.4 mg/lb (9.7 to 11.9 mg/kg) IM is recommended
for such procedures as dentistry, treatment of
abscesses, foreign body removal and related
types of surgery; 4.8 to 5.7 mg/lb (10.6 to
12.5 mg/kg) for minor procedures requiring
mild to moderate analgesia, such as repair of
lacerations, castrations and other procedures of
short duration. Initial dosages of 6.5 to 7.2 mg/
lb (14.3 to 15.8 mg/kg) are recommended for
ovario hysterectomy and onychectomy. When
supplemental doses of TELAZOL are required,
such individual supplemental doses should be
given in increments that are less than the initial
dose, and the total dose given (initial dose plus
supplemental doses) should not exceed the
maximum allowable safe dose of 32.7 mg/lb
(72 mg/kg). (See Animal Safety.)

General Dosing Information

Fasting prior to induction of general anesthesia with
TELAZOL is not essential; however, when preparing
for elective surgery, it is advisable to withhold food
for at least 12 hours prior to TELAZOL administration.
As with other injectable anesthetic agents, the
individual response to TELAZOL is somewhat
varied, depending upon the dose, general physical
condition and age of the patient, duration of the
surgical procedure, and any preanesthetics used.
Therefore, recommendations for dosage regimens
cannot be fixed absolutely. Specific dosage
requirements must be determined by evaluation
of the health status and condition of the patient
and of the procedure to be performed.
Recovery varies with the age and physical
condition of the animal and the dose of TELAZOL
administered. Recovery is extended with high
dose or multiple injections, particularly in cats.

Intramuscular injection in dogs and cats:
There may be pain on injection. This is especially
prevalent in cats.
Following a single, deep intramuscular injection
of TELAZOL in cats and dogs, onset of anesthetic
effect usually occurs within 5 to 12 minutes.
Muscle relaxation is optimum for approximately
the first 20 to 25 minutes after TELAZOL is
administered, and then diminishes.
Repeated doses increase the duration of the
effect of TELAZOL but may not further diminish
muscle tone. The quality of anesthesia with
repeated doses varies because the ratio of the two
components within the animal’s body changes
with each injection. This is due to the difference
in the rates of metabolism and elimination of the
two components. The quality of anesthesia will
be improved and more predictable if the entire
dose is given as a single injection rather than in
several doses. The best method of evaluating
the depth of TELAZOL anesthesia is to monitor
the patient for deliberate conscious response to
nociceptive stimuli.
If adequate anesthesia is not produced by the
recommended dosage regimen, supplemental
anesthesia or another agent is indicated. This
includes the use of barbiturates and volatile
anesthetics. When used concurrently with TELAZOL
the dosage of these agents should be reduced.

PREPARATION OF SOLUTION FOR ADMINISTRATION

To each vial add 5 mL sterile water for injection,
USP. Slight agitation will facilitate complete
reconstitution. The resultant solution will contain
100 mg total TELAZOL per one milliliter (50 mg
tiletamine and 50 mg zolazepam per mL).
Discard unused solution after 7 days when stored
at room temperature or after 56 days when kept
refrigerated. Only use clear solution. Color of
solution may vary from colorless to light amber.

CONTRAINDICATIONS

The use of TELAZOL is contraindicated in dogs and cats with pancreatic disease. TELAZOL is excreted predominantly by the kidneys. Preexistent renal pathology or impairment of renal function may be expected to result in prolonged duration of anesthesia. TELAZOL should not be used in dogs and cats with severe cardiac or pulmonary dysfunction. Because the teratogenic potential of TELAZOL is unknown, it should not be used in pregnant bitches or queens at any stage of pregnancy. Also, a study has shown that TELAZOL crosses the placental barrier and produces respiratory depression in the newborn; therefore, its use for Cesarean section is contraindicated.

WARNINGS

FOR USE IN DOGS AND CATS ONLY.

When using TELAZOL for induction of anesthesia,
patients should be continuously monitored.
Facilities for the maintenance of a patent airway,
artificial ventilation and oxygen supplementation
should be available.
Pulmonary edema has been reported to occur in
cats with the use of TELAZOL. Signs and symptoms
include dyspnea, lethargy, anorexia and abnormal
behavior. Deaths have been reported occasionally
in severely affected individuals. Cats should be
observed closely for any signs and symptoms
which may suggest pulmonary edema so that
appropriate therapy may be instituted.
The principal route of excretion of both
components in the cat is the urine; therefore,
TELAZOL is not recommended for use in cats
suffering from renal insufficiency.
Balance studies in dogs indicated extensive
biotransformation of both components with less
than 4% of the dose excreted unchanged in the
urine.
TELAZOL is excreted predominantly by the
kidneys. Preexistent renal pathology or
impairment of renal function may be expected to
result in prolonged duration of anesthesia.
Phenothiazine-derivative drugs should not
be used with TELAZOL at dosages indicated
for intramuscular (IM) injection because the
combination produces respiratory and myocardial
depression, hypotension and hypothermia.
The safe use of TELAZOL in pregnant animals
or on reproduction has not been established.
TELAZOL crosses the placental barrier and causes
respiratory depression in the neonate.

PRECAUTIONS

The dosage of TELAZOL should be reduced in
geriatric dogs and cats, in animals in debilitated
condition and in animals with impairment of
renal function. Death has occurred in both cats
and dogs following intramuscular TELAZOL
administration. Preexisting pulmonary disease,
renal disease (see Contraindications and
Warnings) and shock were causally implicated at
necropsy; however, death was drug attributable
in at least one dog (of 1072) and one cat (of 1095).
Intravenous TELAZOL has been demonstrated
to be safe in a field study in dogs when used in
conjunction with phenothiazine-derivative drugs
(acepromazine) administered at dosages from
0.04-0.06 mg/kg IM.
Cats and smaller dogs with small body masses
in relation to large body surfaces should be
protected from heat loss during TELAZOL
anesthesia. Body temperature should be
monitored, and supplemental heat may be
required to control hypothermia. As with
other anesthetics, it is prudent to provide for
hemostasis during any surgical procedure.
During TELAZOL anesthesia, athetoid movement
may occur. This athetosis should not be mistaken
for lack of anesthesia nor is it indicative of lack
of analgesia. Do not give additional anesthesia
in an attempt to abolish the athetoid movement.
Efforts to eliminate athetoid movement with
additional doses of TELAZOL can result in
anesthetic overdosage.
TELAZOL does not abolish laryngeal, pharyngeal,
pinnal, palpebral, and pedal reflexes, and may
not be adequate as the sole anesthetic for
surgical procedures in these areas. Endotracheal
tubes are not well tolerated in connection with TELAZOL anesthesia in the cat and their use may
result in impaired respiration. After removal of
the tube, normal respiration should resume.
The stimulation of surgical procedures aids in
maintaining adequate ventilation. The anesthetized
patient must be monitored throughout the
procedure, and if cardiopulmonary problems do
occur, measures must be taken to assure that
alveolar ventilation and cardiovascular functions are
maintained.
The eyes normally remain open with the pupils
dilated. The use of a bland ophthalmic ointment is
advisable to protect the corneas from desiccation.
The concurrent use of chloramphenicol will
prolong the duration of anesthesia in cats.
Copious salivation may occur during TELAZOL
anesthesia. Ptyalism may be controlled in dogs
and cats by administering atropine sulfate, USP,
0.02 mg/lb (0.04 mg/kg) body weight (IV, IM,
or SC) as concurrent medication. Exaggerated
swallowing, reflex action and accumulation of
saliva may give rise to vomiting and retching.

ADVERSE REACTIONS

For Restraint and Minor Procedures of Short
Duration Requiring Mild to Moderate
Analgesia
Respiratory depression may occur following
administration of high doses of TELAZOL. If at any
time respiration becomes excessively depressed
and the animal becomes cyanotic, resuscitative
measures should be instituted promptly. Adequate
pulmonary ventilation using either oxygen or room
air is recommended as a resuscitative measure.
Adverse reactions reported include emesis during
emergence, excessive salivation, transient apnea,
vocalization, erratic recovery and prolonged
recovery, excessive tracheal and bronchial
secretions when atropine sulfate, was not given
before anesthesia, involuntary muscular twitching,
hypertonicity, cyanosis, cardiac arrest, pulmonary
edema and muscle rigidity during surgical
procedures. Central nervous system stimulation and
convulsions have also been reported. Tachycardia
frequently occurs, particularly in the dog. This rise
in heart rate usually lasts about 30 minutes. Either
hypertension or hypotension may also occur.
Insufficient anesthesia has been reported in dogs.
Death has been reported in dogs and cats following
TELAZOL administration.

Intravenous Induction of Anesthesia followed by
Maintenance with Inhalant Anesthesia in Dogs
In a field study to assess the effectiveness and
safety of TELAZOL administered intravenously
at 1-2 mg/lb (2.2-4.4 mg/kg) for the induction of
anesthesia followed by maintenance with inhalant
anesthesia in dogs, 144 dogs were intravenously
administered TELAZOL (See Effectiveness).
Sixteen adverse reactions occurred during the
study: nystagmus (5), emesis (4), diarrhea (2), and
one occurrence each of hypersalivation, urticarial,
anorexia, hyperthermia, and lethargy. All adverse
reactions resolved by the end of the study.
Physiologic abnormalities related to general
anesthesia were transient and not severe.
Post-induction apnea (time from induction to
first inspiration ≥30 seconds) was observed in
49.3% of dogs across all treatment groups with a
mean duration of one minute. The highest overall
frequency and duration of post-induction apnea
was in the alpha2-agonist + opioid groups.
Overall, 36 dogs received assisted ventilation.
Assisted ventilation was needed most frequently
early in the procedure (at procedure start,
possibly after an apneic period) then decreased
in frequency as the procedure continued.
Sixteen dogs experienced oxygen saturation
(SpO2) ≤90 mmHg: 7 in the alpha2-agonist +
opioid groups, 6 in the phenothiazine + opioid
groups, and 3 in the opioid alone groups.
Twenty-five dogs had a temperature ≥103°F
during the study, with 12 of these occurring
prior to preanesthetic administration only. Of the
remaining 13 dogs, 7 were in the alpha2-agonist +
opioid groups, 5 were in the opioid alone groups,
and 1 in the phenothiazine + opioid groups.
One dog was reported with hyperthermia as an
adverse reaction in the alpha2-agonist + opioid
treatment groups. The dog became excitable
during recovery and its temperature elevated to
105.7°F. Hyperthermia resolved with treatment
of IV fluids and cooling.

Twenty-seven dogs experienced temperatures
≤96°F at one or more timepoints. Most dogs
received supplemental heat during surgery.
Fifty-nine dogs had mean blood pressure
(BP) values ≤60 mmHg. These values are
spread among all treatment groups. No dogs
were reported with adverse reactions due to
hypotension or hypertension in any dose groups.
Elevated or low BP values were transient.
Ventricular premature depolarizations were
noted in 3 dogs in the alpha2-agonist + opioid
group. This transient rhythm disturbance is
not uncommon in dogs receiving alpha2-
agonists or inhalant anesthetics. One dog in the
phenothiazine + opioid group showed transient
ST depression that could have been due to
cardiac hypoxia. All dogs recovered normally.
For a copy of the Safety Data Sheet (SDS) or
to report adverse reactions call Zoetis Inc. at
1-888-963-8471. Additional information can be
found at www.Zoetis.US.com.
For additional information about adverse drug
experience reporting for animal drugs, contact
FDA at 1-888-FDA-VETS or http://www.fda.gov/
reportanimalae.

CLINICAL PHARMACOLOGY

Mechanism of Action

TELAZOL is a rapid-acting anesthetic combination
of tiletamine hydrochloride and zolazepam
hydrochloride. Tiletamine hydrochloride is a
dissociative anesthetic agent whose pharmacologic
action is characterized by profound analgesia,
normal pharyngeal-laryngeal reflexes and
cataleptoid anesthesia. The anesthetic state
produced does not fit into the conventional
classification of stages of anesthesia, but instead
TELAZOL produces a state of unconsciousness
which has been termed “dissociative’’ anesthesia in
that it appears to selectively interrupt association
pathways to the brain before producing somesthetic
sensory blockade.
Cranial nerve and spinal reflexes remain active;
however, these reflexes must not be confused
with inadequate anesthesia. Analgesia results
from apparent selective interruption of sensory
inputs to the brain and usually persists after the
anesthetic effect has subsided.
Protective reflexes, such as coughing and
swallowing, are maintained under tiletamine
anesthesia. Other reflexes, e.g., corneal, pedal,
are maintained during tiletamine anesthesia,
and should not be used as criteria for judging
depth of anesthesia. The eyes normally remain
open with the pupil dilated. It is suggested that
a bland ophthalmic ointment be applied to the
cornea if anesthesia is to be prolonged.
Used alone, tiletamine hydrochloride does
not provide adequate muscle relaxation for
abdominal surgical procedures. When combined
with zolazepam hydrochloride, good muscle
relaxation is generally attained during the phase
of deep surgical anesthesia.

Pharmacokinetics
The pharmacokinetics of TELAZOL injectable
solution was evaluated in 12 healthy adult
Beagle dogs, following a single intravenous (IV)
administration of 2.2 mg/kg bodyweight, which
is equivalent to 1.1 mg/kg for both tiletamine
hydrochloride and zolazepam hydrochloride.
After administration of 2.2 mg/kg TELAZOL IV,
the initial mean concentration of tiletamine (C0)
was 1018 ng/mL, the systemic clearance (CL)
was 6223 mL/kg/h, the area under the curve to
the last measured concentration (AUC 0-last) was
178 ng*hr/mL, and steady state volume of
distribution (Vss) was 3250 mL/kg. The mean
elimination half-life of tiletamine was 0.87 hours.
For zolazepam, the mean C0 was 2594 ng/mL, CL
was 1993 mL/kg/h and Vss was 604 mL/kg. The mean
elimination half-life of zolazepam was 0.41 hours.
The mean C0 and AUC0-t(last) were approximately
2.5 and 3 times, respectively, greater for zolazepam
than for tiletamine. However, the mean half-life
(T1/2) of tiletamine was approximately 2.5 times
longer than for zolazepam, resulting in quantifiable
plasma concentrations up to 2 hours longer.
Pretreatment with an alpha-2 agonist or
phenothiazine followed by inhalant isoflurane
has been shown to increase in the initial
concentration of both tiletamine and zolazepam.

EFFECTIVENESS

Dogs
Preanesthesia
In a field study conducted at 6 veterinary hospitals,
144 dogs of various breeds, ranging in age from
4 months to 14 years (mean age 5 years) and
body weights from 1.2- 85.5 kg, were enrolled for
completion of a veterinary procedure requiring
anesthesia. Dogs were preanesthetized with a
phenothiazine + opioid, an opioid alone, or an
alpha2-agonist + opioid at the study Investigator’s
discretion based on individual patient needs.
Approximately 20 minutes later, dogs were
intravenously administered TELAZOL at 1-2 mg/lb
(2.2-4.4 mg/kg) ‘to effect’ of anesthesia and
were intubated. After induction, dogs received
either isoflurane or sevoflurane for anesthetic
maintenance for at least 30 minutes. Procedures
conducted included dental prophylaxis with or
without extractions (64), ovariohysterectomy
(31), castration (18), and mass removal (14).
Upon completion of the procedure, dogs were
monitored in recovery for 4 hours, then followed at
home for 2-4 days, monitoring for the presence of
abnormal clinical signs.
Of 144 dogs enrolled in the study, 142 (98.6%)
were successfully intubated after intravenous
administration of TELAZOL at a mean dosage of
1.2 mg/lb (2.7 mg/kg). The mean dosage range was
lowest in the alpha2-agonist + opioid preanesthetic
treatment group (0.9 mg/lb; 2 mg/kg) and highest
in the opioid alone preanesthetic group (1.8 mg/lb;
3.9 mg/kg).
Overall induction quality evaluated on a scale
of acceptable, intermediate, or unacceptable
was acceptable in 131/142 (91.6%) dogs and
intermediate in 12/143(8.4%) dogs. On a scale of
good, fair, or poor, study participants rated the
quality of recovery from anesthesia as good in
75% of dogs (118/144) and fair in 18.1% (26/144).
In an overall assessment of anesthesia, considering
induction, maintenance, and recovery, was scored
as excellent or good in 128/144 (88.9%) of dogs.
Three dogs (2.1%) were rated with an overall
assessment of anesthesia as poor, and for these
dogs, recovery was also rated poor. Physiologic
measurements of heart rate, respiratory rate,
body temperature, oxygen saturation, and blood
pressure during anesthetic induction, maintenance,
and recovery showed that the administration of
TELAZOL did not severely impact these variables.
A variety of concomitant treatments were used
during the study including intravenous fluid
solutions, non-steroidal anti-inflammatory
medications, antimicrobials, and antiparasitics that
were consistent with routine canine practice.

ANIMAL SAFETY

TELAZOL has a wider margin of safety in cats
than in dogs. Dogs have survived repeated
IM dosage regimens of 13.6 mg/lb (30 mg/kg)
(maximum safe dose) for eight successive days.
This is approximately two times the maximum
recommended therapeutic dose. Cats have
survived IM dosage regimens of up to 32.7 mg/
lb (72 mg/kg) (maximum safe dose) on alternate
days for seven episodes. This is 4.6 times the
maximum recommended therapeutic dose for
cats. However, these reports should not obviate
prudent anesthetic practices. Some degree of
tolerance has been reported. This tolerance
appears to be species-variable.

Cats

In cats, the duration of effect of zolazepam exceeds
that of tiletamine so that as the animal recovers
there is a greater degree of tranquilization than
anesthetization. There is a slight lowering of blood
pressure during the first hour after injection.
Heart rate and electrocardiogram readings are
unaffected by TELAZOL (tiletamine and zolazepam
for injection). Arterial pO2 levels are decreased
three minutes after injection but usually return to
normal within 15 to 35 minutes.

Dogs
In dogs, the duration of effect of tiletamine
exceeds that of zolazepam so there is a lesser
degree of tranquilization than anesthetization in
this species. The total effect of TELAZOL in dogs is
of shorter duration than in cats.
Following administration of TELAZOL in dogs, a
marked, persistent tachycardia occurs within two
minutes following either 4.5 or 9 mg/lb (10 or
20 mg/kg) TELAZOL intramuscularly. Stroke volume
decreases proportionately to the increased rate
at the 4.5 mg/lb (10 mg/kg) dose, with little
change in net cardiac output. There is an initial
increase in systolic blood pressure, with a slight
drop in pressure within five minutes. The systolic
blood pressure remains at this decreased level
throughout the duration of the anesthetic effect.
Diastolic pressure increases throughout this same
period. Following a 9 mg/lb (20 mg/kg) dose
of TELAZOL in dogs, the relationship between
stroke volume and heart rate is disproportionate,
with a resultant substantial decrease in cardiac
output. Contractility and mean blood pressure are
decreased, indicating direct myocardial depression.
Ventricular function is adequate. During surgical
manipulations, tachycardia and hypertension may
be observed, and may be brought on by sympathetic
reaction to painful stimuli. Epinephrine is markedly
less arrhythmogenic in animals under TELAZOL
anesthesia than in those under halothane anesthesia.
During TELAZOL anesthesia, the assurance of
a patent airway is greatly enhanced by virtue
of maintaining pharyngeal-laryngeal reflexes.
During the first 15 minutes after intramuscular
administration of 9 mg/lb (20 mg/kg) of TELAZOL,
the respiratory rate is doubled while the tidal
volume is decreased to less than one-half of control
values. Arterial pO2 levels also decrease. This may
be evidenced by hypoxemia and cyanosis. The
pulmonary function usually returns to normal within
35 minutes after the administration of TELAZOL.

Preanesthetic Compatibility Study in Dogs
Six healthy Beagle dogs (3 males and 3 females),
at least 8 months of age, ranging in body
weight between 5.6 and 9.4 kg, were fitted
with a telemetry device that captured systemic
arterial blood pressures, electrocardiogram, and
body temperature. Each dog received a total of
6 treatments with at least a 7-day washout between
periods. During each period, dogs received
1 of the following 6 preanesthetics prior to the
TELAZOL administration: placebo (0.9% saline),
acepromazine low dose (0.1 mg/kg body weight
[BW]), acepromazine high dose (1.1 mg/kg BW),
dexmedetomidine low dose (125 mcg/m2 body
surface area [BSA]), dexmedetomidine high dose
(375 mcg/m2 BSA), or butorphanol (0.4 mg/kg BW).
Blood samples were collected at intubation, end
of isoflurane administration, and after anesthesia
when the dogs were able to walk. Plasma
concentrations of tiletamine and zolazepam were
measured using a validated method. Preanesthetic
treatment with high dose acepromazine and both
high and low doses of dexmedetomidine resulted
in substantial increases in plasma concentrations
of tiletamine and zolazepam at intubation. The
increase in the tiletamine plasma concentrations
was approximately 2X higher for the high dose of
acepromazine and 2.7 to 4.5X higher for the low
and high doses of dexmedetomidine, respectively,
compared to saline. The increase in zolazepam
plasma concentrations was 1.5X higher for the
high dose acepromazine, and 1.8 to 2.8X higher
for the low and high doses of dexmedetomidine,
respectively, compared to saline.
No information on the dose-sparing of TELAZOL
was obtained during the study because the dogs
were given the full initial half-dose (2.2 mg/kg) and
not actually administered TELAZOL ‘to effect’. The
average total dose of test article administered to
the dogs was 2.6 mg/kg for the saline group and
2.2 mg/kg for the other treatment groups. One
dog (saline group) required more than the initial
2.2 mg/kg bolus to achieve intubation at the first
attempt.
Without preanesthesia (saline group), dogs
retained a strong cough reflex, chewing motions,
tachycardia and increased muscle tone during
intubation. With preanesthesia, half of the dogs
in the high dose dexmedetomidine group had
no laryngeal reflex response to intubation and
all experienced post-intubation apnea. The postintubation
apnea suggests that the 2.2 mg/kg dose
of TELAZOL was higher than necessary in some
groups.
All dogs in all treatment groups achieved successful
anesthetic plane following TELAZOL administration
and were intubated and induced to isoflurane
anesthesia uneventfully. The quality of intubation,
and occurrence and severity of adverse reactions
(e.g., apnea and bradypnea) following TELAZOL
administration and intubation revealed differences
among preanesthetic treatment groups. The
cardiovascular and respiratory changes observed
were typical of each preanesthetic medication used
in combination with TELAZOL. Acepromazine and
isoflurane administration decreased arterial blood
pressure. Dexmedetomidine decreased heart rate.
Intubation transiently increased heart rate and/or
blood pressure (sympathetic stimulations). Mild to
severe respiratory depression was observed after
TELAZOL administration and each preanesthetic
agent. Adverse reactions were manageable with
appropriate care.

STORAGE CONDITIONS

Store at controlled room temperature 20° to 25°C (68° to 77°F). Discard unused solution after 7 days when stored at room temperature or after 56 days when kept refrigerated. Only use clear solution. Color of solution may vary from colorless to light amber.

HOW SUPPLIED

TELAZOL (tiletamine and zolazepam for injection) is available in individual vials of 5 mL solution when reconstituted. The addition of 5 mL diluent produces a solution containing the equivalent of 50 mg tiletamine base, 50 mg zolazepam base and 57.7 mg mannitol per milliliter.
10 mL vial -100 mg/mL total (equivalent to 50 mg/mL tiletamine and 50 mg/mL zolazepam) when reconstituted

Approved by FDA under NADA # 106-111
zoetis
Distributed by:
Zoetis Inc.
Kalamazoo, MI 49007
Revised: September 2022
40040578